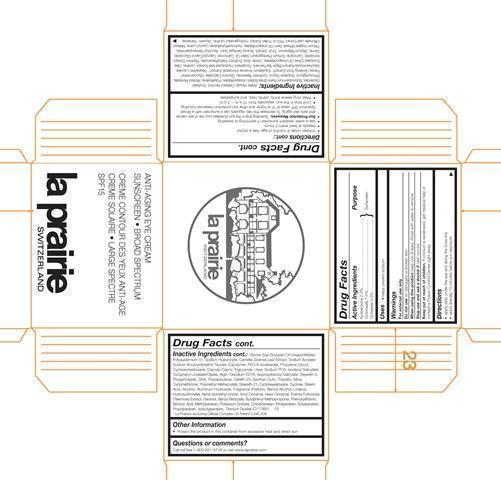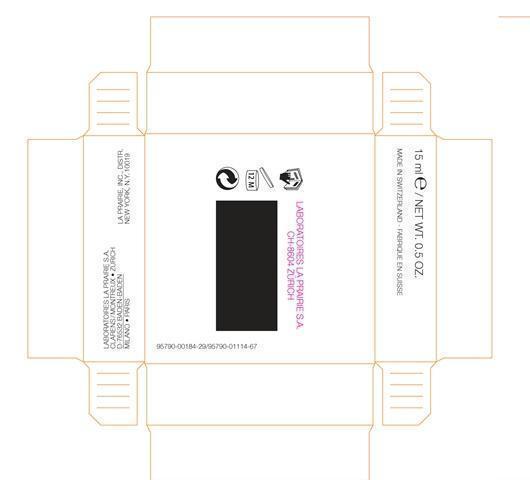 DRUG LABEL: Anti-Aging Eye Broad Spectrum SPF 15
NDC: 68807-303 | Form: CREAM
Manufacturer: Temmentec Ag
Category: otc | Type: HUMAN OTC DRUG LABEL
Date: 20170103

ACTIVE INGREDIENTS: AVOBENZONE 2 g/100 mL; OCTINOXATE 7.5 g/100 mL; OCTISALATE 3 g/100 mL
INACTIVE INGREDIENTS: WATER; CETOSTEARYL ALCOHOL; SHEA BUTTER; HIGH DENSITY POLYETHYLENE; MYRISTYL MYRISTATE; DIETHYLENE GLYCOL MONOETHYL ETHER; BUTYLENE GLYCOL; SYNTHETIC WAX (1200 MW); GLYCERYL CAPRATE; ASIAN GINSENG; EQUISETUM ARVENSE TOP; HESPERETIN LAURATE; TOCOPHEROL; LECITHIN, SOYBEAN; URSOLIC ACID; CARNOSINE; ECHIUM PLANTAGINEUM SEED OIL; CARBOMER 934; CAPRYLYL/CAPRYL OLIGOGLUCOSIDE; SERINE; MILK THISTLE; ACACIA; ASCORBYL TETRAISOPALMITATE; HYDROXYETHYL CELLULOSE (100 MPA.S AT 2%); LAUROYL LYSINE; MELISSA OFFICINALIS LEAF; POLYETHYLENE GLYCOL 400; HYDROGENATED SOYBEAN LECITHIN; GLYCERIN; TREHALOSE; POLYQUATERNIUM-51 (2-METHACRYLOYLOXYETHYL PHOSPHORYLCHOLINE/N-BUTYL METHACRYLATE; 3:7); HYALURONATE SODIUM; GREEN TEA LEAF; SODIUM ACRYLATE/SODIUM ACRYLOYLDIMETHYLTAURATE COPOLYMER (4000000 MW); PEG-6 ISOSTEARATE; PROPYLENE GLYCOL; CYCLOMETHICONE 5; MEDIUM-CHAIN TRIGLYCERIDES; UREA; SODIUM PYRROLIDONE CARBOXYLATE; SODIUM ALGINATE; EDETATE DISODIUM; ISOPROPYLBENZYL SALICYLATE; STEARETH-2; CETETH-20; XANTHAN GUM; TRIACETIN; MICA; CYCLOMETHICONE; STEARETH-21; CYCLOMETHICONE 6; SUCROSE; STEARIC ACID; ALCOHOL; ALUMINUM HYDROXIDE; BENZYL ALCOHOL; LINALOOL, (+)-; HYDROXYCITRONELLAL; GERANIOL; BENZYL BENZOATE; BUTYLPHENYL METHYLPROPIONAL; PHENOXYETHANOL; BENZOIC ACID; METHYLPARABEN; POTASSIUM SORBATE; CHLORPHENESIN; ETHYLPARABEN; BUTYLPARABEN; PROPYLPARABEN; ISOBUTYLPARABEN; TITANIUM DIOXIDE

Anti-Aging Eye Cream SPF 15

Active Ingredients Purpose

Avobenzone 2.0% Sunscreen

Octinoxate 7.5% Sunscreen

Octisalate 3.0% Sunscreen

Uses

helps prevent sunburn

Keep out of reach of children. If product is swallowed, get medical help or contact a Poison Control Center right away.

Stop use and ask a doctor if rash occurs

warnings

For external use only

Do not use on damaged or broken skin

When using this product keep out of eyes. Rinse with water to remove.

Directions

apply daily under the eye and along the brow line

apply liberally 15 minutes before sun exposure

children under 6 months of age: Ask a doctor

reapply at least every 2 hours

use a water resistant sunscreen of swimming or sweating

Sun Protection Measures.

Spending time in the sun increases your risk of skin cancer

and early skin aging. To decrease this risk, regularly use a sunscreen with a Broad

Spectrum SPF value of 15 or higher and other sun protection measures including:

Limit time in the sun, especially from 10 a.m. – 2 p.m.

Wear long-sleeve shirts, pants, hats, and sunglasses

Inactive Ingredients:

Water (Aqua), Cetearyl Alcohol, Soybean Glycerides, Butyrospermum Parkii (Shea Butter) Unsaponifiables, Polyethylene, Myristyl Myristate, Ethoxydiglycol, Butylene Glycol, Synthetic Beeswax, Glyceryl Caprylate, Glycoproteins, Panax Ginseng Root Extract, Equisetum Arvense (Horsetail) Extract, Hesperetin Laurate, Saccharomyces/Xylinum/Black Tea Ferment, Tocopherol, Hydrolyzed Malt Extract, Lecithin, Olea Europaea (Olive) Oil Unsaponifiables, Ursolic Acid, Erythrityl Triethylhexanoate, Plankton Extract, Ilomastat, Carnosine, Echium Plantagineum Seed Oil, Carbomer, Caprylyl/Capryl Glucoside, Serine, Silybum Marianum Fruit Extract, Acacia Senegal Gum, Ascorbyl Tetraisopalmitate, Triticum Vulgare (Wheat) Germ Oil Unsaponifiables, Hydroxyethylcellulose, Lauroyl Lysine, Melissa Officinalis Leaf Extract, PEG-8, Pollen Extract, Hydrogenated Lecithin, Glycerin, Trehalose, Glycine Soja (Soybean) Oil Unsaponifiables, Polyquaternium-51, Sodium Hyaluronate, Camellia Sinensis Leaf Extract, Sodium Acrylate/Sodium Acryloyldimethyl Taurate Copolymer, PEG-6 Isostearate, Propylene Glycol, Cyclopentasiloxane, Caprylic/Capric Triglyceride, Urea, Sodium PCA, Isodecyl Salicylate, Tocopheryl Linoleate/Oleate, Algin, Disodium EDTA, Isopropylbenzyl Salicylate, Steareth-2, Phospholipids, DNA, Polyisobutene, Ceteth-20, Xanthan Gum, Triacetin, Mica, Cyclomethicone, Polymethyl Methacrylate, Steareth-21, Cyclohexasiloxane, Sucrose, Stearic Acid, Alcohol, Aluminum Hydroxide, Fragrance (Parfum), Benzyl Alcohol, Linalool, Hydroxycitronellal, Alpha-Isomethyl Ionone, Amyl Cinnamal, Hexyl Cinnamal, Evernia Furfuracea (Treemoss) Extract, Geraniol, Benzyl Benzoate, Butylphenyl Methylpropional, Phenoxyethanol, Benzoic Acid, Methylparaben, Potassium Sorbate, Chlorphenesin, Ethylparaben, Butylparaben, Propylparaben, Isobutylparaben, Titanium Dioxide (CI 77891)

PACKAGE LABEL

Anti-Aging Eye Cream Sunscreen Broad Spectrum

Creme Contour Des Yeux Anti-Age Creme Solaire Large Spectre SPF 15

La Prairie Switzerland 15 ml/ Net Wt. 0.5 Oz